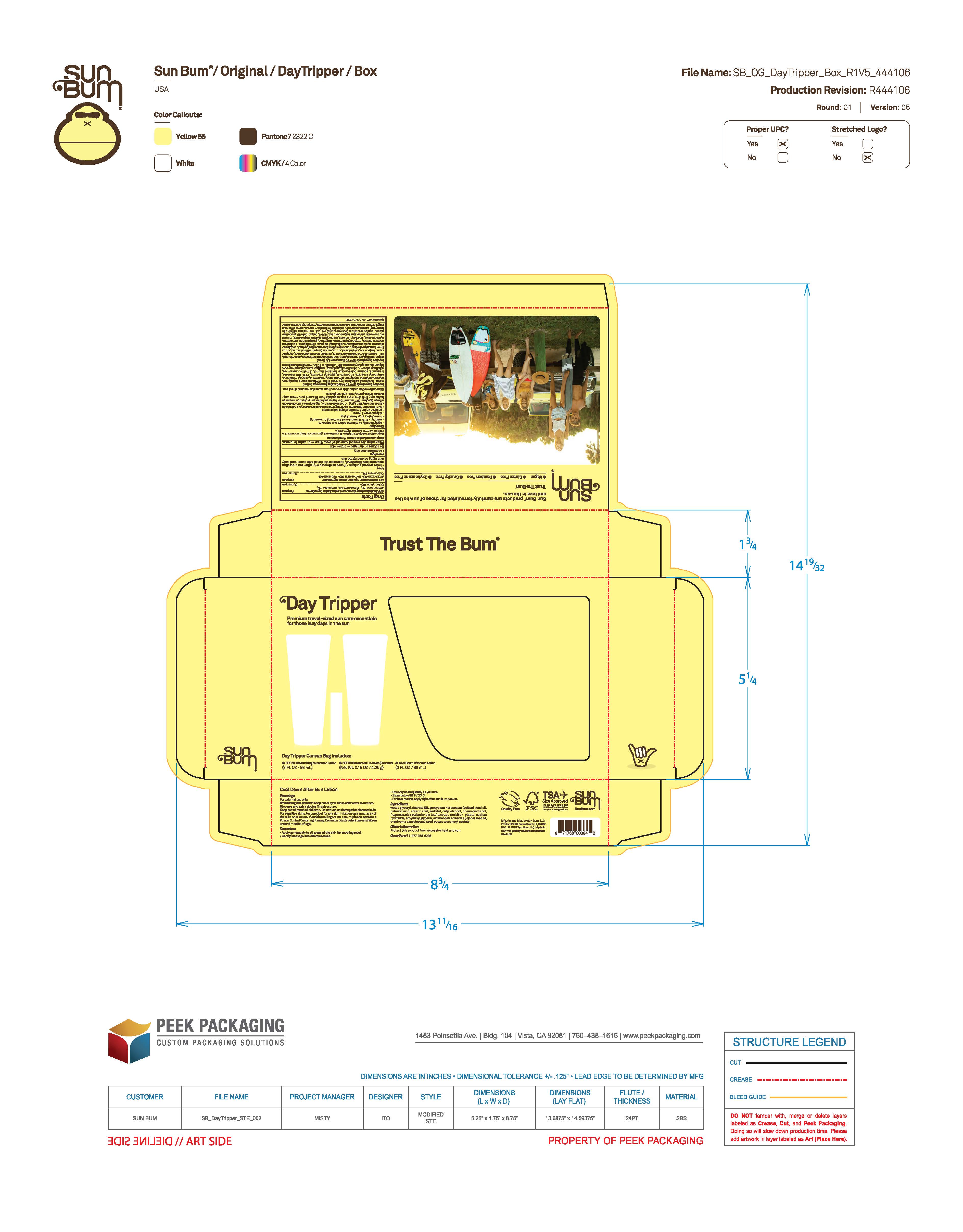 DRUG LABEL: Sun Bum Day Tripper - SPF 30 Moisturizing Sunscreen 3 OZ
NDC: 69039-814 | Form: LOTION
Manufacturer: Sun Bum, LLC
Category: otc | Type: HUMAN OTC DRUG LABEL
Date: 20250820

ACTIVE INGREDIENTS: HOMOSALATE 50 mg/1 mL; OCTOCRYLENE 100 mg/1 mL; AVOBENZONE 30 mg/1 mL; OCTISALATE 30 mg/1 mL
INACTIVE INGREDIENTS: BUTYLOCTYL SALICYLATE; DIMETHICONE; CAPRYLYL METHICONE; TRIDECETH-6; SODIUM POLYACRYLATE (8000 MW); ETHYLHEXYLGLYCERIN; .ALPHA.-TOCOPHEROL ACETATE; EDETATE DISODIUM; METHYLISOTHIAZOLINONE; GLYCERYL STEARATE; BEHENYL ALCOHOL; DIMETHYL CAPRAMIDE; TRIMETHYLSILOXYSILICATE (M/Q 0.6-0.8); HYDRATED SILICA; PEG-100 STEARATE; POLYAMINOPROPYL BIGUANIDE; LUVISET 360; WATER; POLYESTER-8 (1400 MW, CYANODIPHENYLPROPENOYL CAPPED); ETHYLHEXYL STEARATE; XANTHAN GUM; BHT; VP/HEXADECENE COPOLYMER

Sun Bum Day Tripper and Sun Bum Day Tripper Amazon - SPF 30 Sunscreen 3 OZ

Active Ingredients

AVOBENZONE 3%, HOMOSALATE 5%, OCTISALATE 3%, OCTOCRYLENE 10%

Purpose

Sunscreen

Uses

• helps prevent sunburn • if used as directed with other sun protection measures, (see Directions) decreases the risk of skin cancer and early skin aging caused by the sun

Warnings

For external use only

Do not use on damaged or broken skin

When using this product keep out of eyes. Rinse with water to remove.

Stop use and ask a doctor if rash occurs

Keep out of reach of children. If swallowed, get medical help or contact a Poison Control Center immediately.

Warnings

Keep Out Of Reach Of Children

Directions

• apply liberally 15 minutes before sun exposure

• reapply: • after 80 minutes of swimming or sweating • immediately after towel drying • at least every 2 hours

• children under 6 months of age: ask a doctor

• Sun Protection Measures. Spending time in the sun increases your risk of skin cancer and early skin aging. To decrease this risk, regularly use a sunscreen with a Broad Spectrum SPF value of 15 or higher and other sun protection measures including:

• limit time in the sun, especially from 10 a.m.- 2 p.m.

• wear long-sleeved shirts, pants, hats and sunglasses

Directions

• apply liberally 15 minutes before sun exposure

Other Information

protect this product from excessive heat and direct sun

Inactive Ingredients

WATER, BUTYLOCTYL SALICYLATE, HYDRATED SILICA, VP/HEXADECENE COPOLYMER, STYRENE/ACRYLATES COPOLYMER, DIMETHICONE, POLYESTER-8, CAPRYLYL METHICONE, ETHYLHEXYL STEARATE, TRIDECETH-6, GLYCERYL STEARATE, PEG-100 STEARATE, FRAGRANCE, SODIUM POLYACRYLATE, BEHENYL ALCOHOL, DIMETHYL CAPRAMIDE, ETHYLHEXYLGLYCERIN, TRIMETHYLSILOXYSILICATE, XANTHAN GUM, POLYAMINOPROPYL BIGUANIDE, TOCOPHEROL ACETATE, BHT, DISODIUM EDTA, METHYLISOTHIAZOLINONE

Questions?

1-877-978-6286